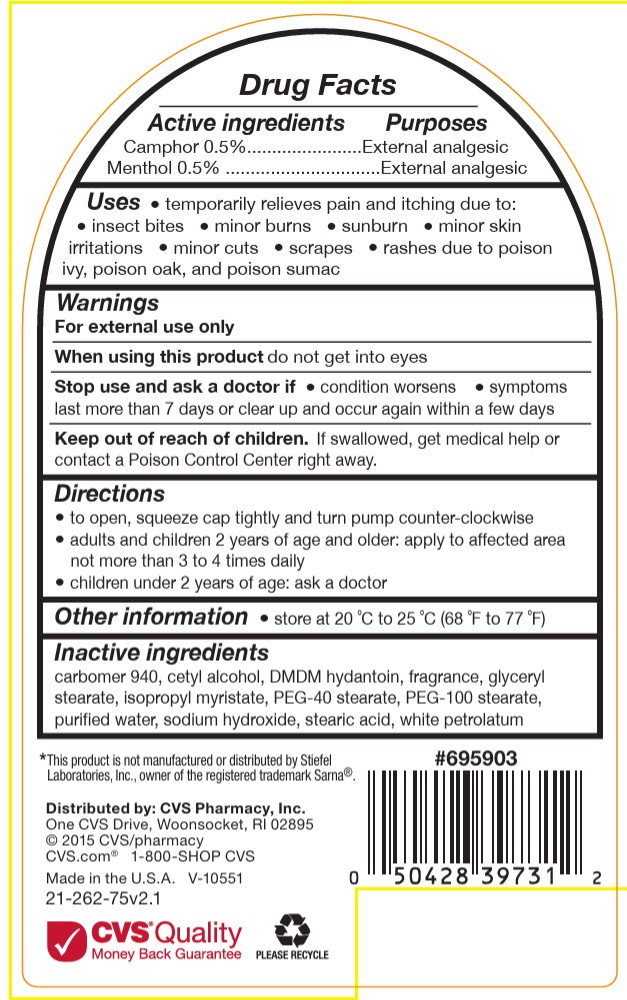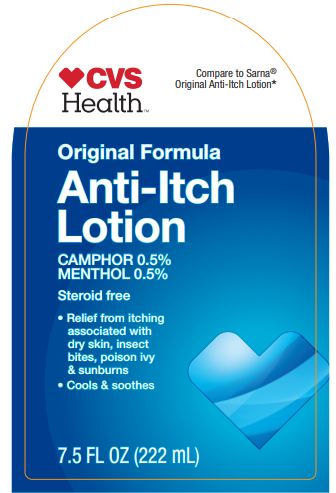 DRUG LABEL: CVS Anti-Itch
NDC: 69842-626 | Form: LOTION
Manufacturer: CVS
Category: otc | Type: HUMAN OTC DRUG LABEL
Date: 20251119

ACTIVE INGREDIENTS: CAMPHOR (SYNTHETIC) 0.5 g/100 g; MENTHOL 0.5 g/100 g
INACTIVE INGREDIENTS: ISOPROPYL MYRISTATE; WATER; PEG-40 STEARATE; CETYL ALCOHOL; PEG-100 STEARATE; STEARIC ACID; DMDM HYDANTOIN; SODIUM HYDROXIDE; CARBOMER 940; PETROLATUM

CVS Original Anti-Itch Lotion

ACTIVE INGREDIENT

Camphor 0.5%

Menthol 0.5%

INDICATIONS AND USAGE

temporary relieves pain and itching due to:

insect bites

minor burns

sunburn

minor skin irritations

minor cuts

scrapes

rashes due to poison ivy, poison oak, and poison sumac

WARNINGS

For external use only

Do not use

on large areas of the body

with any other product containing diphenhydramine, even one taken by mouth

ASk doctor before use

on chicken pox

on measles

when using this product

do not get into eyes

Stop Use and ask doctor if

condition worsens

symptoms last more than 7 days or clear up and occur again within a few days

Keep out of reach of children

If swallowed, get medical help or contact a Poison Control Center right away.

PURPOSE

Anti-itch

External analgesic

Directions

to open, squeeze cap tightly and turn pump counter-clockwise

adults and children 2 years and older: apply to affected area not more than 3 to 4 times daily

children under 2 years: ask a doctor

Other information

store at 20 °C to 25 °C (68 °F to 77 °F)

INACTIVE INGREDIENT

carbomer 940, cetyl alcohol, DMDM hydantoin, fragrance, glyceryl stearate, isopropyl myristate, PEG-40 stearate,
PEG-100 stearate, purified water, sodium hydroxide, stearic acid, white petrolatum

Uses

- Removed dries the oozing or weeping of rashes due to poison ive, poison oak, and poison sumac.

PACKAGE LABEL

CVS Health

Compare to Sarna Original Anti-Itch lotion

Original Formula Anti-Itch Lotion

Camphor 0.5%

Menthol 0.5%

Steroid Free

Relief from itching associated with dry skin, insectr bites, poison ivy and Sunburn

Cools and Soothes